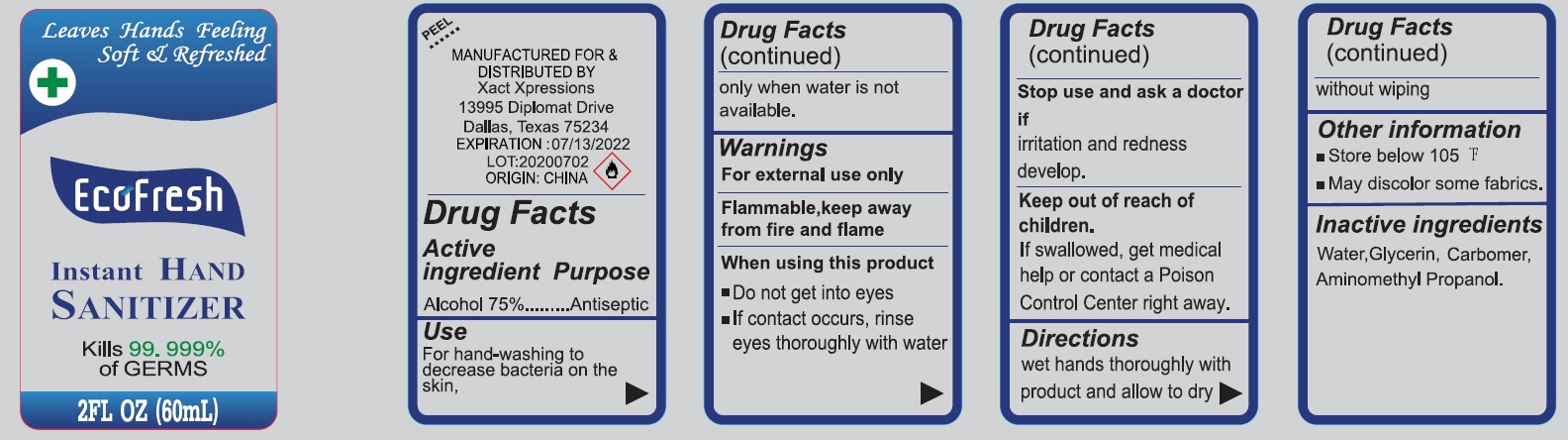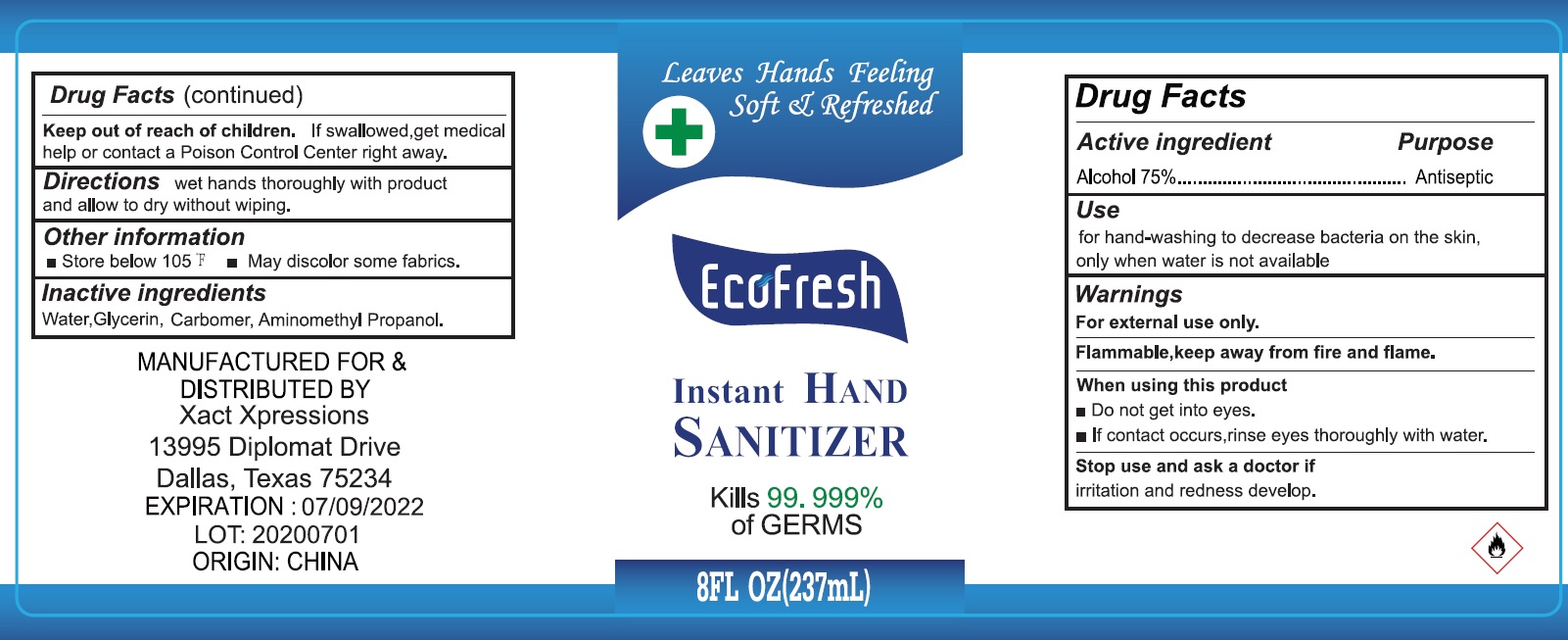 DRUG LABEL: Instant HAND SANITIZER
NDC: 79524-000 | Form: GEL
Manufacturer: Xact Xpressions
Category: otc | Type: HUMAN OTC DRUG LABEL
Date: 20231026

ACTIVE INGREDIENTS: ALCOHOL 0.75 mL/1 mL
INACTIVE INGREDIENTS: WATER; GLYCERIN; CARBOMER HOMOPOLYMER, UNSPECIFIED TYPE; AMINOMETHYLPROPANOL

Instant HAND SANITIZER

Active ingredient

Alcohol 75%

Purpose

Antiseptic

Use

For hand-washing to decrease bacteria on the skin, only when water is not available.

Warnings

For external use only

Flammable,keep away from fire and flame

When using this product

- Do not get into eyes
- If contact occurs, rinse eyes thoroughly with water

Stop use and ask a doctor if

irritation and redness develop.

Keep out of reach of children.

If swallowed, get medical help or contact a Poison Control Center right away.

Directions

wet hands thoroughly with product and allow to dry without wiping

Other information

- Store below 105 °F
- May discolor some fabrics.

Inactive ingredients

Water, Glycerin, Carbomer, Aminomethyl Propanol.